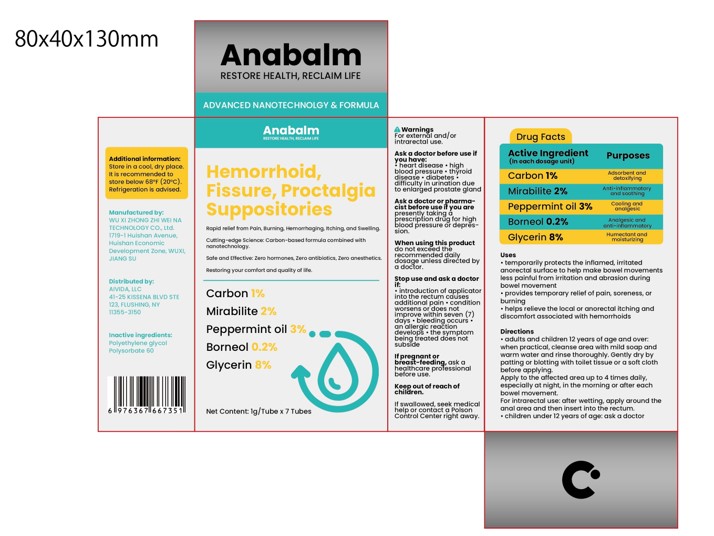 DRUG LABEL: Hemorrhoid, Fissure, ProctalgiaSuppositories
NDC: 84533-001 | Form: SUPPOSITORY
Manufacturer: WU XI ZHONG ZHI WEI NA TECHNOLOGY CO., Ltd.
Category: otc | Type: HUMAN OTC DRUG LABEL
Date: 20260114

ACTIVE INGREDIENTS: PEPPERMINT OIL 0.2 g/100 g; GLYCERIN 8 g/100 g; ACTIVATED CHARCOAL 1 g/100 g; SODIUM SULFATE 2 g/100 g; BORNEOL 3 g/100 g
INACTIVE INGREDIENTS: POLYETHYLENE GLYCOL, UNSPECIFIED; POLYSORBATE 60

84533-001 Hemorrhoid, Fissure, Proctalgia Suppositories

ACTIVE INGREDIENT

Carbon 1%
Mirabilite 2%
Peppermint oil 0.2%
Borneol 3%

Glycerin 8%

PURPOSE

Adsorbent and detoxifying
Anti-inflammatory and soothing
Cooling and analgesic
Analgesic and anti-inflammatery
Humectant and moisturizing

Keep out of reach ofchildren.
lf swallowed, seek medicalhelp or contact a PolsonControl Center right away.

INDICATIONS AND USAGE

temporarily protects the inflamed, irritatedanorectal surface to help make bowel movementsless painful from irritation and abrasion duringbowel movement
*provides temporary relief of pain, soreness, orburning*helps relieve the local or anorectal itching anddiscomfort associated with hemorrhoids

WARNINGS

For external and/or intrarectal use.

DOSAGE AND ADMINISTRATION

adults and children 12 years of age and over:when practical, cleanse area with mild soap andwarm water and rinse thoroughly.Gently dry bypatting or blotting with toilet tissue or a soft clothbefore applying.Apply to the affected area up to 4 times daily,especially at night, in the morning or after eachbowel movement.For intrarectal use: after wetting, apply around theanal area and then insert into the rectum..children under 12 years of age: ask a doctor

STORAGE AND HANDLING

Additionalinformation:store in a cool, dry place.It is recommended tostore below 68°F(20°C)Refrigeration is advised.

INACTIVE INGREDIENT

Polyethylene Glycol
POLYSORBATE 60